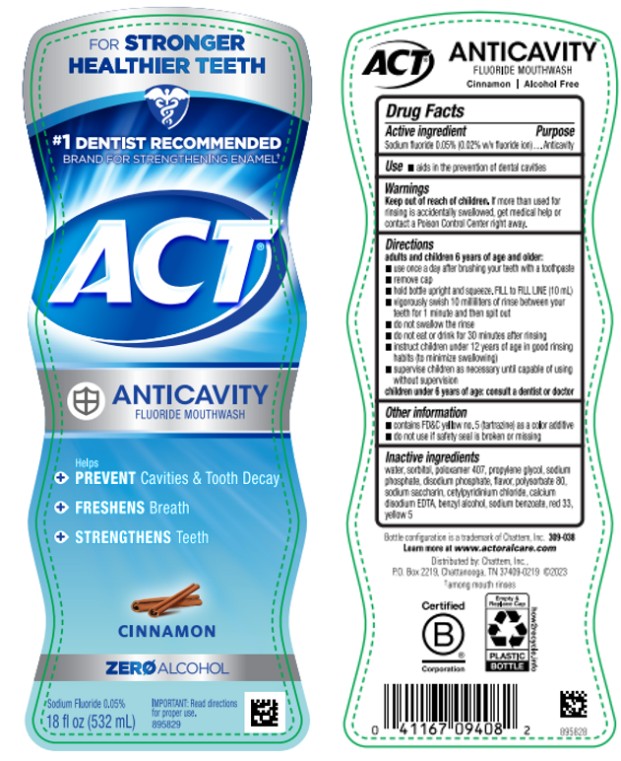 DRUG LABEL: ACT Anticavity Fluoride Cinnamon
NDC: 41167-0940 | Form: RINSE
Manufacturer: Chattem, Inc.
Category: otc | Type: HUMAN OTC DRUG LABEL
Date: 20260112

ACTIVE INGREDIENTS: SODIUM FLUORIDE 0.2 mg/1 mL
INACTIVE INGREDIENTS: WATER; SORBITOL; POLOXAMER 407; PROPYLENE GLYCOL; SODIUM PHOSPHATE; SODIUM PHOSPHATE, DIBASIC, ANHYDROUS; POLYSORBATE 80; SACCHARIN SODIUM; CETYLPYRIDINIUM CHLORIDE; EDETATE CALCIUM DISODIUM ANHYDROUS; BENZYL ALCOHOL; SODIUM BENZOATE; D&C RED NO. 33; FD&C YELLOW NO. 5

ACT Anticavity Fluoride Rinse Cinnamon

Drug Facts

Active ingredient

Sodium fluoride 0.05% (0.02% w/v fluoride ion)

Purpose

Anticavity

Use

- aids in the prevention of dental cavities

Warnings

Keep out of reach of children.

If more than used for rinsing is accidentally swallowed, get medical help or contact a Poison Control Center right away.

Directions

adults and children 6 years of age and older:

- use once a day after brushing your teeth with a toothpaste
- remove cap
- hold bottle upright and squeeze. Fill to FILL LINE (10 mL)
- vigorously swish 10 milliliters of rinse between your teeth for 1 minute and then spit out
- do not swallow the rinse
- do not eat or drink for 30 minutes after rinsing
- instruct children under 12 years of age in good rinsing habits (to minimize swallowing)
- supervise children as necessary until capable of using without supervision

children under 6 years of age: consult a dentist or doctor

Other information

- contains FD&C yellow no. 5 (tartrazine) as a color additive
- do not use if safety seal is broken or missing

Inactive ingredients

water, sorbitol, poloxamer 407, propylene glycol, sodium phosphate, disodium phosphate, polysorbate 80, sodium saccharin, flavor, cetylpridinium chloride, calcium disodium EDTA, benzyl alcohol, sodium benzoate, red 33, yellow 5 (309-098)

Learn more at www.ACTFLUORIDE.com

PRINCIPAL DISPLAY PANEL

#1 DENTIST RECOMMENDED
ACT
ANTICAVITY
FLUORIDE MOUTHWASH
Alcohol Free
CINNAMON
18 fl. oz. (532 mL)